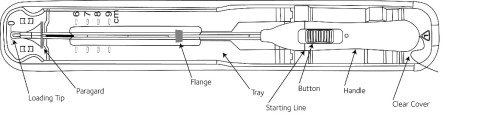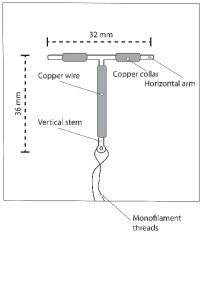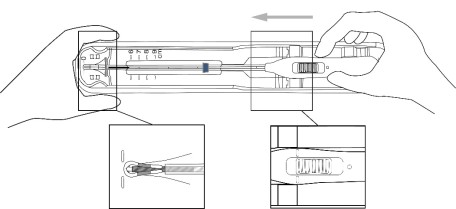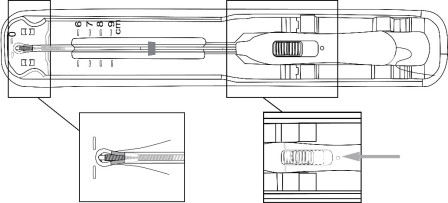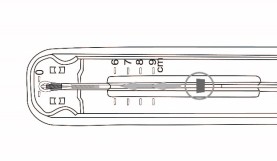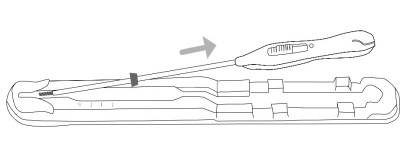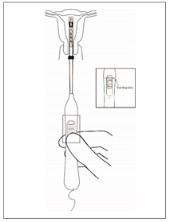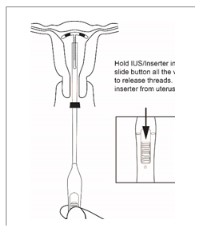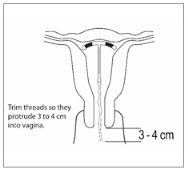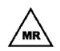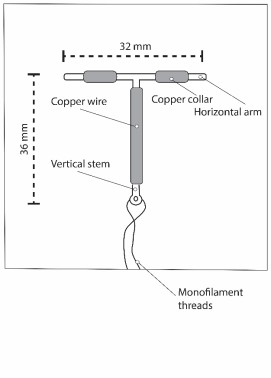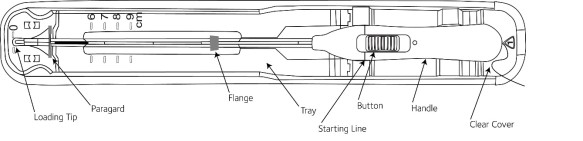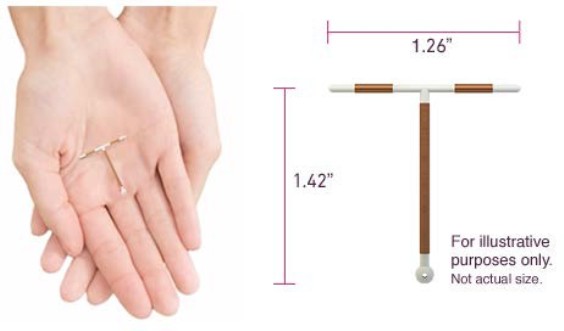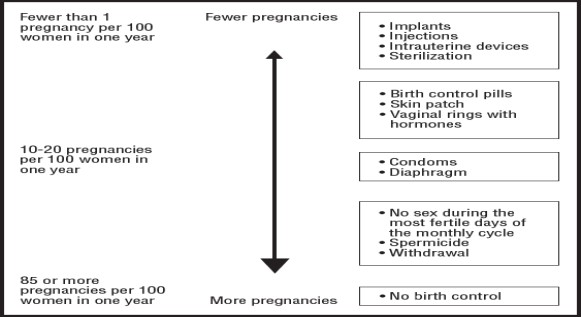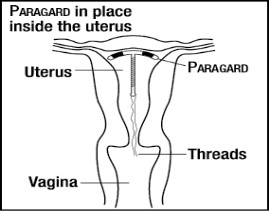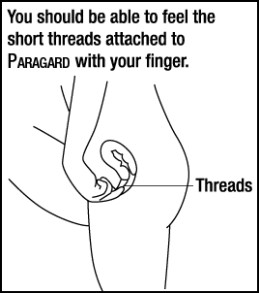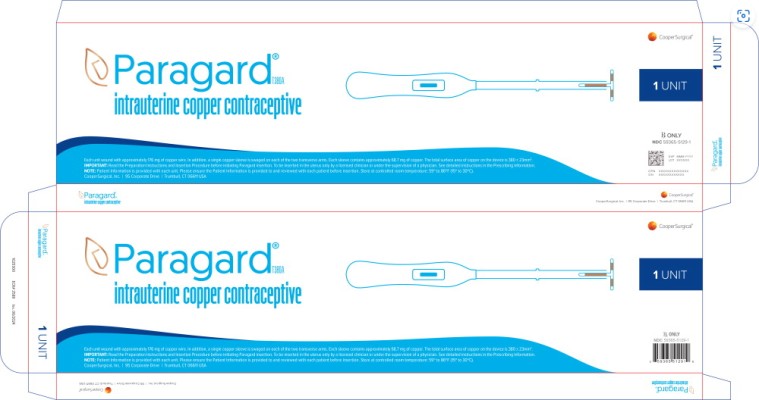 DRUG LABEL: ParaGard T 380A
NDC: 59365-5129 | Form: INTRAUTERINE DEVICE
Manufacturer: CooperSurgical, Inc.
Category: prescription | Type: HUMAN PRESCRIPTION DRUG LABEL
Date: 20240601

ACTIVE INGREDIENTS: COPPER 313.4 mg/1 1
INACTIVE INGREDIENTS: POLYETHYLENE GLYCOL, UNSPECIFIED; BARIUM SULFATE

HIGHLIGHTS OF PRESCRIBING INFORMATION

These highlights do not include all the information needed to use PARAGARD® safely and effectively. See full prescribing information for PARAGARD.
PARAGARD (intrauterine copper contraceptive)
Initial U.S. Approval: 1984

RECENT MAJOR CHANGES

Dosing and Administration (2)……………………………………06/2024

1 INDICATIONS AND USAGE

Paragard is a copper-containing intrauterine system (IUS) indicated for prevention of pregnancy in females of reproductive potential for up to 10 years. (1)

2 DOSAGE AND ADMINISTRATION

- Insert a single Paragard at the fundus of the uterine cavity. Remove Paragard no later than 10 years from the date of insertion. (2.1)
- Insert and remove Paragard only if you are a healthcare provider trained on these procedures. (2.1)
- See the Full Prescribing Information for recommended timing of insertion preparation instructions, insertion procedures, postplacement management, and instructions on removing Paragard. (2.2, 2.3, 2.4, 2.5, 2.6)
- Following the insertion, examine the patient after her first menses to confirm Paragard is still in place. (2.5)

3 DOSAGE FORMS AND STRENGTHS

One sterile, T-frame IUS containing copper consisting of a T-shaped polyethylene frame with a total exposed copper surface area of 380 ± 23 mm², (approximately 176 mg of wire wrapped around the vertical stem and an approximately 68.7 mg collar placed on each side of the horizontal arm) packaged with a sterile pre-assembled inserter as a single-use, disposable device in a tray. (3, 16)

4 CONTRAINDICATIONS

- Pregnancy or suspicion of pregnancy (4)
- Abnormalities of the uterus resulting in distortion of the uterine cavity (4)
- Acute pelvic inflammatory disease (PID) (4)
- Postpartum endometritis or postabortal endometritis in past 3 months (4)
- Known or suspected uterine or cervical malignancy (4)
- Uterine bleeding of unknown etiology (4)
- Untreated acute cervicitis or vaginitis or other lower genital tract infection (4)
- Conditions associated with increased susceptibility to pelvic infections (4)
- Wilson’s disease (4)
- A previously placed IUD or IUS that has not been removed (4)
- Hypersensitivity to any component of Paragard including copper or any trace elements present in the copper components of Paragard (4)

5 WARNINGS AND PRECAUTIONS

- Ectopic Pregnancy: Promptly evaluate women who become pregnant for ectopic pregnancy while using Paragard. (5.1)
- Risks with Intrauterine Pregnancy: Increased risk of spontaneous abortion, septic abortion, premature delivery, sepsis, septic shock and death if pregnancy occurs. Remove Paragard if pregnancy occurs with Paragard in place. (5.2)
- Sepsis: Group A streptococcal infection has been reported; strict aseptic technique is essential during insertion (5.3)
- Pelvic Inflammatory Disease (PID) and Endometritis: Before using Paragard, consider the risks of PID and endometritis. Promptly assess and treat patients with signs and symptoms of PID. (5.4)
- Embedment: Surgical removal may be necessary. (5.5)
- Perforation: May reduce contraceptive effectiveness and require surgery. Risk is increased if inserted in lactating women and may be increased if inserted in women with fixed, retroverted uteri or noninvoluted uteri. (5.6)
- Expulsion: Partial or complete expulsion may occur. Remove a partially expelled Paragard. (5.7)
- Bleeding patterns: May be altered and result in heavier and longer bleeding with spotting. (5.9)
- MRI Safety Information: Patients using Paragard can be safely scanned with MRI only under certain conditions. (5.10)

6 ADVERSE REACTIONS

Adverse reactions reported in clinical trials include: anemia, backache, dysmenorrhea, dyspareunia, expulsion (complete or partial), prolonged menstrual flow, menstrual spotting, pain and cramping, and vaginitis. (6.1)

To report SUSPECTED ADVERSE REACTIONS, contact CooperSurgical, Inc. at 1-877-727-2427 or FDA at 1-800-FDA-1088 or www.fda.gov/medwatch.

FULL PRESCRIBING INFORMATION

1 INDICATIONS AND USAGE

Paragard is indicated for prevention of pregnancy in females of reproductive potential for up to 10 years.

2 DOSAGE AND ADMINISTRATION

2.1 Important Dosage and Administration Instructions

- Paragard should only be inserted by a healthcare provider trained in Paragard’s insertion procedures, because insertion for Paragard is different from that used for other intrauterine systems. Healthcare providers should become thoroughly familiar with the product, product educational materials, product insertion instructions, and prescribing information before attempting insertion of Paragard.
- Insert one Paragard at the fundus of the uterine cavity [see Dosage and Administration (2.4)].
- Remove Paragard on or before 10 years from the date of insertion [see Dosage and Administration (2.6)].
- May replace Paragard at the time of removal with a new Paragard if continued contraceptive protection is desired.
- Before considering use of Paragard, make sure that the female is an appropriate candidate for Paragard. Exclude pregnancy (consider the possibility of ovulation and conception) prior to use [see Contraindications (4) and Warnings and Precautions (5.2)].

2.2 Timing of Insertion

Refer to Table 1 for recommended timing of Paragard insertion.

Table 1: Recommended Timing of Paragard Insertion
Clinical Situation | Recommended Timing of Paragard Insertion
1. Start Paragard in females not currently using contraception | At any time during the menstrual cycle.
2. Switch to Paragard from an oral, transdermal, or vaginal form of hormonal contraception or an injectable progestin contraceptive | At any time during the menstrual cycle; discontinue the previous method.
3. Switch to Paragard from a contraceptive implant or other intrauterine system | Same day the implant or IUS is removed (insert at any time during the menstrual cycle).
4. Insert Paragard after abortion or miscarriage | Immediately after abortion, although immediate placement has a slightly higher risk of expulsion than placement at other times. Insertion after second trimester abortion is associated with a higher risk of expulsion than insertion after a first trimester abortion.
5. Insert Paragard after Childbirth | May insert immediately postpartum. Insertion before uterine involution is complete, which may not occur until the second postpartum month, has been associated with increased risk of expulsion [see Warnings and Precautions (5.6,5.7)]. There appears to be an increased risk of perforation in lactating women [see Warnings and Precautions (5.6)].

Note: The inserter provided with Paragard (see Figure 1) and the Insertion Procedure described in subsection 2.4 are not applicable for immediate insertion after childbirth. For immediate insertion post childbirth, remove the inserter and Paragard from the tray, move the button forward and then completely back to release the Paragard unit from the inserter and insert Paragard.

2.3 Preparation Instructions

Read the Preparation Instructions and Insertion Procedure before initiating Paragard insertion.

Before insertion:

- Do NOT remove the inserter from the tray before the arms are loaded into the insertion tube. The tray will be used to fold the Paragard arms down and load the IUS into the inserter.
- Use strict aseptic techniques throughout preparation [see Warnings and Precautions (5.4)].
- Prepare placement tools (e.g., speculum, cotton swab, tenaculum, uterine sound, scissors, and forceps).
- Consider use of an analgesic.
- Establish the size and position of the uterus by performing a bi-manual examination.
- Insert a speculum and, using a cotton swab, cleanse the cervix and vagina with an antiseptic solution.
- Apply a tenaculum to the cervix and use gentle traction to align the cervical canal with the uterine cavity.
- Gently insert a sterile uterine sound to measure the depth of the uterine cavity. The uterus should sound to a depth of 6 to 9 cm except when inserting Paragard immediately postabortion or immediately postpartum.
  - Insertion of Paragard may be associated with pain and/or bleeding, vasovagal reactions (e.g. syncope, bradycardia), or seizure, especially in patients with a predisposition to these conditions.
  - Insertion into a uterine cavity measuring less than 6 cm may increase the incidence of expulsion, bleeding, pain, and perforation.
  - If cervical stenosis is encountered, avoid undue force. Dilators and analgesia/local anesthesia may be helpful in this situation.

2.4 Insertion Procedure

Follow the insertion instructions exactly as described to ensure proper placement and avoid early release of Paragard from the inserter.

- Use strict aseptic techniques throughout the insertion procedure [see Warnings and Precautions (5.4)].

Step 1: Opening the Sterile Paragard Package

- Place the package containing Paragard (face-up) on a flat sterile field (see Figure 1). Open the pouch from the handle end where the arrow on the Placement Guide says “OPEN”.

Figure 1: Inserter

Figure 2: Paragard Intrauterine System (IUS)

- Remove the clear cover from the tray (not shown).
- Confirm that the top of the button is located at the starting line on the handle prior to loading Paragard.
- The inserter should remain in the tray until Paragard T-Arms are loaded.

Do not slide the button on the handle before folding the arms in the tray.

Do not repeatedly slide the button forward and back as this may cause slack in the threads and may result in an unsuccessful placement.

Step 2: Loading Paragard into the Inserter

- Using sterile gloves, place one hand on the distal end of the tray and the other on the inserter handle. Slide the handle completely forward so that the Paragard advances into the Loading Tip folding the T-Arms of Paragard against the stem (see Figure 3).

Figure 3: Folding Tips of T-Arms of Paragard using Loading Tip

- Once the T-Arms are folded against the stem, slide the button on the handle completely forward to advance the insertion tube over the tips of the T-Arms (see Figure 4). Only the tips of the T-Arms should be in the insertion tube. Do not advance beyond the copper collars.

IMPORTANT: Do not leave the T-Arms of Paragard bent for more than 5 minutes, as the arms may not open properly.

Figure 4: Inserting Tips of T-Arms into Insertion Tube

Step 3: Adjusting the Flange

- Once the above steps are completed and Paragard is in the insertion tube, adjust the blue flange. The tray is marked with centimeters and can be used to set the flange to the correct depth (see Figure 5).
- Adjust the flange so the distance from the top of Paragard (where it protrudes from the inserter) to the top of the flange is equal to the pre-measured uterine depth.

Figure 5: Adjusting the Blue Flange to sound depth

Step 4: Removing Inserter from Tray

- Ensure the button remains in the forward position.
- To remove the inserter from the tray, gently lift the handle out of the tray, then gently slide the inserter back and lift out of the tray. (see Figure 6).
- Upon removal from the tray, verify and rotate the blue flange as needed so that the horizontal arms of Paragard and the long axis of the blue flange and handle lie in the same horizontal plane to ensure the arms open in the proper direction.
- Confirm that both T-Arms are captured within the insertion tube.

Figure 6: Removal of Inserter from Tray

Step 5: Inserting Paragard to the Fundus

- To orient the uterus in an axial position, apply gentle traction to the tenaculum. While holding the button forward, pass the loaded inserter through the cervical canal until the Paragard reaches the fundus of the uterus. This will ensure placement of Paragard at the highest possible position within the uterus.
- The blue flange should be at the cervix in the horizontal plane. The button should remain in the forward position (see Figure 7).

Figure 7: Inserter with Paragard at Uterine Fundus

Step 6: Releasing Paragard and Withdrawing Inserter

- Release the arms of Paragard by holding the handle steady and sliding the button all the way down (and you may feel a click). Do not stop at the starting line as it is not used for deployment.
- This releases the threads and the T-Arms of Paragard high in the uterine fundus (see Figure 8).

Figure 8: Release T-Arms of Paragard at Uterine Fundus

- Gently and slowly withdraw the inserter from the uterus and cervical canal.
- Only the threads should be visibly protruding from the cervix (see Figure 9). Trim the threads so that 3 to 4 cm protrude into the vagina.
- Measure and note the length of threads, date of placement and Paragard lot number.
- Discard the used inserter – do not attempt to re-use the inserter because it is a single use device.
- If you suspect that Paragard is not in the correct position, check placement (with ultrasound, if necessary). If Paragard is not positioned completely within the uterus, remove it and replace it with a new Paragard. Do not reinsert an expelled or partially expelled Paragard.

Figure 9: Appropriate Paragard Placement in Uterus

2.5 Postplacement Management of Paragard

Following placement:

- Examine the female after her first menses to confirm that Paragard is still in place. You should be able to visualize or feel only the threads. The length of the visible threads may change with time. However, no action is needed unless you suspect partial expulsion, perforation, pregnancy, or breakage.
- If you cannot find the threads in the vagina, check that Paragard is still in the uterus. The threads can retract into the uterus or break, or Paragard can break, perforate the uterus, or be expelled. Gentle probing of the cavity, x-ray, or sonography may be required to locate Paragard.
- Remove Paragard if it has been partially expelled or perforated the uterus [see Warnings and Precautions (5.6, 5.7)].

Do not reinsert a used Paragard.

2.6 Removal of Paragard

Timing of Removal

- Paragard can be removed at any time prior to 10 years after insertion.
- Remove Paragard no later than 10 years after insertion. A new Paragard can be inserted at the time of removal if continued contraceptive protection is desired.

Removal Instructions

- Use a speculum and visualize the cervix.
- Remove Paragard with forceps, pulling gently on the exposed threads. The arms of Paragard will fold upwards as it is withdrawn from the uterus.
- If removal cannot be accomplished by gentle pulling, consider checking Paragard location and assess for embedment and perforation (with imaging, if necessary).
- Breakage or embedment of Paragard in the myometrium can make removal difficult [see Warnings and Precautions, (5.5)]. IUS breakage may be associated with removal. Analgesia, paracervical anesthesia, cervical dilation, alligator forceps or other grasping instrument, or hysteroscopy may assist in removing an embedded Paragard.
- Make sure Paragard is intact upon removal.
- Removal may be associated with some pain and/or bleeding, vasovagal reactions (e.g. syncope, bradycardia), or seizure, especially in patients with a predisposition to these conditions.

3 DOSAGE FORMS AND STRENGTHS

Paragard is a T-frame copper-containing intrauterine system (IUS) consisting of a polyethylene frame with barium sulfate measuring 32 mm horizontally and 36 mm vertically, with approximately 176 mg of copper wire wrapped around the vertical stem and an approximately 68.7 mg copper wire collar placed on each side of the horizontal arm with a total exposed copper surface area is 380 ± 23 mm², packaged with a sterile pre-assembled inserter as a single-use, disposable device in a tray. A monofilament polyethylene thread is tied through the tip of the vertical stem resulting in two white threads, each approximately 36.5 cm in length. Figure 1 displays the contents of the package [see Dosage and Administration (2.3)].

4 CONTRAINDICATIONS

The use of Paragard is contraindicated when one or more of the following conditions exist:

- Pregnancy or suspicion of pregnancy [see Warnings and Precautions (5.1, 5.2) and Use in Specific Populations (8.1)]
- Abnormalities of the uterus resulting in distortion of the uterine cavity
- Acute pelvic inflammatory disease (PID) [see Warnings and Precautions (5.4)]
- Postpartum endometritis or postabortal endometritis in the past 3 months [see Warnings and Precautions (5.4)]
- Known or suspected uterine or cervical malignancy
- Uterine bleeding of unknown etiology
- Untreated acute cervicitis or vaginitis or other lower genital tract infection
- Conditions associated with increased susceptibility to pelvic infections [see Warnings and Precautions (5.4)]
- Wilson’s disease [see Warnings and Precautions (5.8)]
- A previously placed IUD or IUS that has not been removed
- Hypersensitivity to any component of Paragard including to copper or any of the trace elements present in the copper component of Paragard [see Adverse Reactions (6.2) and Description (11)]

5 WARNINGS AND PRECAUTIONS

5.1 Ectopic Pregnancy

Evaluate for possible ectopic pregnancy in any female who becomes pregnant while using Paragard because a pregnancy that occurs with Paragard in place is more likely to be ectopic than a pregnancy in the general population. However, because Paragard prevents most pregnancies, females who use Paragard have a lower risk of an ectopic pregnancy than sexually active females who do not use any contraception.

The incidence of ectopic pregnancy in the clinical trials with Paragard (which excluded females with a previous history of ectopic pregnancy) was approximately 0.06%. Ectopic pregnancy may require surgery and may result in loss of fertility.

5.2 Risks with Intrauterine Pregnancy

If intrauterine pregnancy occurs with Paragard in place and the strings are visible or can be retrieved from the cervical canal, remove Paragard because leaving it in place may increase the risk of spontaneous abortion and preterm labor. Removal of Paragard may also result in spontaneous abortion. In the event of an intrauterine pregnancy with Paragard, consider the following:

Septic Abortion

In females becoming pregnant with an intrauterine system (IUS), including Paragard in place, septic abortion, with septicemia, septic shock, and death, may occur [see Warnings and Precautions (5.3)]. Septic abortion typically requires hospitalization and treatment with intravenous antibiotics. Septic abortion may result in spontaneous abortion or a medical indication for pregnancy termination. A hysterectomy may be required if severe infection of the uterus occurs, which will result in permanent infertility.

Continuation of Pregnancy

If a female becomes pregnant with Paragard in place and if Paragard cannot be removed or the female chooses not to have it removed, warn her that failure to remove Paragard increases the risk of miscarriage, sepsis, premature labor, and premature delivery. Prenatal care should include counseling about these risks and that she should report immediately any flu-like symptoms, fever, chills, cramping, pain, bleeding, vaginal discharge or leakage of fluid, or any other symptom that suggests complications of the pregnancy.

5.3 Sepsis

Severe infection or sepsis, including Group A streptococcal sepsis (GAS), have been reported following insertion of IUSs, including Paragard. In some cases, severe pain occurred within hours of insertion followed by sepsis within days. Because death from GAS is more likely if treatment is delayed, it is important to be aware of these rare but serious infections. Aseptic technique during insertion of Paragard is essential in order to minimize serious infections such as GAS [see Dosage and Administration (2.3)].

5.4 Pelvic Inflammatory Disease and Endometritis

Insertion of Paragard is contraindicated in the presence of known or suspected Pelvic Inflammatory Disease (PID) or endometritis [see Contraindications (4)]. IUSs, including Paragard, have been associated with an increased risk of PID, most likely due to organisms being introduced into the uterus during insertion. In the clinical trials with Paragard, the incidence of PID that resulted in the removal of Paragard was approximately 0.1% [see Clinical Studies (14)].

Counsel women who receive Paragard to notify a healthcare provider if they have complaints of lower abdominal or pelvic pain, odorous discharge, unexplained bleeding, fever, or genital lesions or sores. In such circumstances, perform a pelvic examination promptly to evaluate for possible pelvic infection.

Remove Paragard in cases of recurrent PID or endometritis, or if an acute pelvic infection is severe or does not respond to treatment.

PID can have serious consequences, such as tubal damage (leading to ectopic pregnancy or infertility), hysterectomy, sepsis, and death.

Females at Increased Risk for PID

PID or endometritis are often associated with a sexually transmitted infection (STI) and Paragard does not protect against STIs. The risk of PID or endometritis is greater for females who have multiple sexual partners, and also for females whose sexual partner(s) have multiple sexual partners. Females who have had PID or endometritis are at increased risk for a recurrence or re-infection. In particular, ascertain whether a female is at increased risk of infection (for example, leukemia, acquired immune deficiency syndrome (AIDS), intravenous drug abuse).

Asymptomatic PID

PID or endometritis may be asymptomatic but still result in tubal damage and its sequelae.

Treatment of PID or Endometritis in Patients Using Paragard

Remove Paragard in cases of recurrent endometritis or PID, or if an acute pelvic infection is severe or does not respond to treatment. Prophylactic antibiotics administered at the time of insertion do not appear to lower the incidence of PID.

Promptly assess and treat any female who develops signs or symptoms of PID. Perform appropriate testing for sexually transmitted infection and initiate antibiotic therapy promptly. Paragard does not need to be removed immediately. Reassess the patient in 48-72 hours. If no clinical improvement occurs, continue antibiotics and consider removal of Paragard. If the decision is to remove Paragard, start antibiotics prior to removal to avoid the potential risk for bacterial spread resulting from the removal procedure.

Actinomycosis

Actinomycosis has been associated with IUS use, including Paragard. Symptomatic women with known actinomycosis infection should have Paragard removed and receive antibiotics. Actinomycetes can be found in the genital tract cultures in healthy women without IUSs. The significance of actinomyces-like organisms on a Papanicolaou (PAP) smear in an asymptomatic IUS user is unknown, and this finding alone does not always require IUS removal and treatment. When possible, confirm a PAP smear diagnosis with cultures.

5.5 Embedment

Partial penetration or embedment of Paragard in the myometrium can make removal difficult. In some cases, surgical removal may be necessary. Breakage of an embedded Paragard during non-surgical removal has been reported [see Dosage and Administration (2.6)].

5.6 Perforation

Partial or total perforation of the uterine wall or cervix may occur during insertions, although the perforation may not be detected until sometime later. Perforation may reduce contraceptive efficacy and result in pregnancy. The incidence of perforation during or following Paragard insertion in clinical trials was 0.2% (13 out of 5344).

Delayed detection or removal of Paragard in cases of perforation may result in migration outside the uterine cavity, adhesions, peritonitis, intestinal penetration, intestinal obstruction, abscesses and/or damage to adjacent organs.

A postmarketing safety study conducted in Europe (EURAS IUD) with IUSs, including copper IUSs, demonstrated an increased risk of perforation in lactating women. The risk of perforation may be increased if an IUS, such as Paragard, is inserted when the uterus is fixed, retroverted or not completely involuted during the postpartum period.

If perforation does occur, locate and remove Paragard promptly. Surgery may be required. Preoperative imaging followed by laparoscopy or laparotomy is often required to remove Paragard from the peritoneal cavity.

5.7 Expulsion

Partial or complete expulsion of Paragard has been reported, resulting in the loss of contraceptive protection. The incidence of expulsion in the clinical trials with Paragard was approximately 2.3%. Consider further diagnostic imaging, such as x-ray, to confirm expulsion if the IUS is not found in the uterus.

Paragard has been placed immediately after delivery, although the risk of expulsion may be increased when the uterus is not completely involuted at the time of insertion. Remove a partially expelled Paragard.

5.8 Wilson’s Disease

Paragard may exacerbate Wilson’s disease, a rare genetic disease affecting copper excretion; therefore, the use of Paragard is contraindicated in females of reproductive potential with Wilson’s disease [see Contraindications (4)].

5.9 Bleeding Pattern Alterations

Paragard can alter the bleeding pattern and result in heavier and longer menstrual cycles with intermenstrual spotting.

In two clinical trials with Paragard, there were reports of oligomenorrhea and amenorrhea; however, a causal relationship between Paragard and these events could not be established. Menstrual changes were the most common medical reason for discontinuation of Paragard. Discontinuation rates for pain and bleeding combined were highest in the first year of use and diminished thereafter. The percentage of females who discontinued Paragard because of bleeding problems or pain during these studies ranged from 12% in the first year to 2% in Year 9. Females complaining of heavy vaginal bleeding should be evaluated and treated, and may need to discontinue Paragard [see Adverse Reactions (6.1)].

5.10 Magnetic Resonance Imaging (MRI) Safety Information

Non-clinical testing has demonstrated that Paragard is MR Conditional. A patient with Paragard can be safely scanned in an MR system meeting the following conditions:

- Static magnetic field of 3.0 T or 1.5T
- Maximum spatial field gradient of 4,000 gauss/cm (40 T/m)
- Maximum MR system reported, whole body averaged specific absorption rate (SAR) of 2 W/kg (Normal Operating Mode)

Under the scan conditions defined above, Paragard is expected to produce a maximum temperature rise of less than 0.5º C after 15 minutes of continuous scanning.

In non-clinical testing, the image artifact caused by the system extended less than 5 mm from the implant when imaged with a gradient echo pulse sequence and a 3.0 T MRI system.

5.11 Medical Diathermy

Medical equipment that contain high levels of Radiofrequency (RF) energy such as diathermy may cause health effects (by heating tissue) in females with a metal-containing IUD including Paragard. Avoid using high medical RF transmitter devices in females with Paragard.

6 ADVERSE REACTIONS

The following serious adverse reactions are discussed elsewhere in the labeling:

- Ectopic pregnancy [see Warnings and Precautions (5.1)]
- Intrauterine pregnancy [see Warnings and Precautions (5.2)]
- Septic abortion [see Warnings and Precautions (5.2)]
- Group A Streptococcal Sepsis (GAS) [see Warnings and Precautions (5.3)]
- Pelvic Inflammatory Disease and Endometritis [see Warnings and Precautions (5.4)]
- Embedment [see Warnings and Precautions (5.5)]
- Perforation [see Warnings and Precautions (5.6)]
- Expulsion [see Warnings and Precautions (5.7)]
- Bleeding Pattern Alterations [see Warnings and Precautions (5.9)]

6.1 Clinical Trials Experience

Because clinical trials are conducted under widely varying conditions, adverse reaction rates observed in the clinical trials of a drug cannot be directly compared to rates in the clinical trials of another drug and may not reflect the rates observed in clinical practice.

The data described below reflect exposure in two trials [see Clinical Studies (14)].

- The WHO Study 79914 was a randomized, multicenter, multinational study of copper T IUSs, including Paragard in 1,396 women outside the U.S. In the WHO Study, 100% were parous and the mean age at enrollment was 29 years old.
- The U.S. Composite Study was a meta-analysis that evaluated randomized, double-blind, comparative studies of copper T IUSs, including Paragard in 3,536 women in the U.S. In the U.S. Composite Study, 64% were nulliparous, 49% were nulligravida, 68% were under age 25 at the time of enrollment (median age 23 years old).

Table 2 shows discontinuation rates from the two clinical studies by adverse reaction and year.

Table 2: Summary of Rates* (No. per 100 Subjects) by Year for Adverse Reactions Causing Discontinuation
 | Year
 | 1 | 2 | 3 | 4 | 5 | 6 | 7 | 8 | 9 | 10
Number of Women at Start of Year | 4,932 | 3,149 | 2,018 | 1,121 | 872 | 621 | 563 | 483 | 423 | 325
Expulsion | 5.7 | 2.5 | 1.6 | 1.2 | 0.3 | 0.0 | 0.6 | 1.7 | 0.2 | 0.4
Bleeding/Pain | 11.9 | 9.8 | 7.0 | 3.5 | 3.7 | 2.7 | 3.0 | 2.5 | 2.2 | 3.7
Other Medical Event | 2.5 | 2.1 | 1.6 | 1.7 | 0.1 | 0.3 | 1.0 | 0.4 | 0.7 | 0.3

*Rates were calculated by weighting the annual rates by the number of subjects starting each year for each of the U.S. Composite Study (3536 subjects) and the World Health Organization (1396 subjects) trials.

The following adverse reactions have also been observed: anemia, backache, dysmenorrhea, dyspareunia, complete or partial expulsion, prolonged menstrual flow, menstrual spotting, pain and cramping, and vaginitis.

Study CSIPD-001

The Paragard inserter that enables single-hand insertion was evaluated in Study CSIPD-001. A total of 117 females of reproductive potential aged 18 to 49 years, underwent Paragard insertion and were followed for up to 12 weeks of Paragard use. Subjects were predominantly white (76%), 45% were parous, and 35% were obese. Successful placement of Paragard with first attempt occurred in 91% of the subjects and 99% with two insertion attempts. Adverse reactions of special interest occurring during the study were IUS expulsion (2.6%), vasovagal reaction (2.6%), IUS malposition (1.7%), partial uterine perforation (0.9%), and IUS embedment (0.9%).

6.2 Postmarketing Experience

The following adverse reactions have been identified during post-approval use of Paragard. Because these reactions are reported voluntarily from a population of uncertain size, it is not always possible to reliably estimate their frequency or establish a causal relationship to drug exposure.

Gastrointestinal Disorders: abdominal distension, nausea

General Disorders and Administration Site Conditions: device breakage, pyrexia; copper wire breakage

Immune System Disorders: allergy to metals, hypersensitivity

Infections and Infestations: endometritis/uterine infection

Musculoskeletal and Connective Tissue Disorders: muscle spasms

Nervous System Disorders: dizziness

Reproductive System and Breast Disorders: amenorrhea

Skin and Subcutaneous Tissue Disorders: Stevens-Johnson syndrome

7 DRUG INTERACTIONS

No drug-drug interaction or drug-herbal supplement interaction studies have been conducted with Paragard.

8 USE IN SPECIFIC POPULATIONS

8.1 Pregnancy

Risk Summary

Use of Paragard is contraindicated for use in pregnant females because there is no need for pregnancy prevention in a female who is already pregnant and Paragard may cause adverse pregnancy outcomes. If a female becomes pregnant with Paragard in place, there is an increased risk of miscarriage, sepsis, premature labor, and premature delivery [see Contraindications (4) and Warnings and Precautions (5.1, 5.2)]. Advise the female of the potential risks if pregnancy occurs with Paragard in place.

Published studies on pregnancy outcomes exposed to copper IUSs report up to 27% miscarriage when the IUS was removed compared to 77% miscarriage when the IUS remained in the uterus. Studies on Paragard and birth defects have not been conducted.

8.2 Lactation

Risk Summary

No difference has been detected in concentration of copper in human milk before and after insertion of copper IUSs, including Paragard. There is no information on the effect of copper in a breastfed child or the effect on milk production. The developmental and health benefits of breastfeeding should be considered along with the mother’s clinical need for Paragard and any potential adverse effects on the breastfed child from Paragard.

8.4 Pediatric Use

The safety and effectiveness of Paragard have been established in females of reproductive potential. Efficacy is expected to be the same for postmenarcheal females regardless of age.

Paragard is not indicated in females before menarche.

8.5 Geriatric Use

Paragard has not been studied in women over 65 years of age and is not indicated in this population.

11 DESCRIPTION

11.1 Paragard IUS

Paragard (intrauterine copper contraceptive) is a T-shaped intrauterine system (IUS), measuring 32 mm horizontally and 36 mm vertically, with a 3 mm diameter bulb at the tip of the vertical stem. (See Figure 10) [see Dosage and Administration (2.3)]. A monofilament polyethylene thread is tied through the tip, resulting in two white threads, each approximately 36.5 cm in length, to aid in detection and removal of the intrauterine system. The T-frame is made of polyethylene with barium sulfate to aid in detecting the intrauterine system under x-ray. Paragard also contains copper (approximately 176 mg of wire wrapped around the vertical stem and an approximately 68.7 mg collar placed on each side of the horizontal arm). The total exposed copper surface area is 380 ± 23 mm². One Paragard weighs less than one (1) gram.

Figure 10 – Paragard IUS

Paragard, its components, and the packaging are not made with natural rubber latex.

11.2 Inserter

Paragard is packaged with a sterile pre-assembled inserter as a single-use, disposable device in a tray and in a Tyvek® polyethylene pouch. A moveable blue flange on the insertion tube aids in gauging the depth of insertion through the cervical canal and into the uterine cavity (See Figure 11) [see Dosage and Administration (2.3)].

Figure 11 – Paragard with Inserter

12 CLINICAL PHARMACOLOGY

12.1 Mechanism of Action

Copper continuously released into the uterine cavity contributes to the contraceptive effectiveness of Paragard. Mechanism(s) by which copper enhances contraceptive efficacy include interference with sperm transport and fertilization of an egg, and possibly prevention of implantation.

13 NONCLINICAL TOXICOLOGY

13.1 Carcinogenicity, Mutagenicity, Impairment of Fertility

Adequate long-term studies in animals to assess the carcinogenic potential of a copper-containing IUS have not been performed.

The genotoxic potential of a copper-containing IUS has not been evaluated.

14 CLINICAL STUDIES

The efficacy of Paragard for use in females of reproductive potential for prevention of pregnancy for up to 10 years was demonstrated in two trials:

- WHO Study 79914 was a randomized, multicenter, multinational study of copper T IUSs, including Paragard in 1,396 women outside the U.S. In the WHO study, 100% were parous and the mean age at enrollment was 29 years old.
- The U.S. Composite Study was a meta-analysis that evaluated several randomized, double-blind, comparative studies of copper T IUSs, including the Paragard in 3,536 women in the U.S. In the U.S. study, 64% were nulliparous, 49% were nulligravida; 68% were under age 25 at the time of enrollment (median age 23 years old).

The pregnancy rate in the two clinical studies with Paragard was less than 1 pregnancy per 100 women each year (see Table 3).

Table 3: Pregnancy Rates* (Number of Pregnancies per 100 Women) by Year in the WHO and U.S. Studies
 | Year
 | 1 | 2 | 3 | 4 | 5 | 6 | 7 | 8 | 9 | 10
Pregnancy | 0.7 | 0.3 | 0.6 | 0.2 | 0.3 | 0.2 | 0.0 | 0.4 | 0.0 | 0.0
Number of Women at Start of Year | 4,932 | 3,149 | 2,018 | 1,121 | 872 | 621 | 563 | 483 | 423 | 325

*Rates were calculated by weighting the annual rates by the number of subjects starting each year for each of the U.S. Composite Study (3536 subjects) and the World Health Organization (1396 subjects) trials.

16 HOW SUPPLIED/STORAGE AND HANDLING

Paragard (intrauterine copper contraceptive) is available in cartons of 1 (one) sterile unit (NDC 59365-5129-1).

Each Paragard is white, T-shaped, and measures 32 mm horizontally and 36 mm vertically, with approximately 176 mg of copper wire wrapped around the vertical stem and an approximately 68.7 mg copper wire collar placed on each side of the horizontal arms, and with a monofilament polyethylene thread tied through the tip of the vertical stem [see Dosage and Administration (2.3)]. The T-frame is made of polyethylene with barium sulfate. Each Paragard is packaged with a sterile pre-assembled inserter as a single-use, disposable device in a tray and in a Tyvek® polyethylene pouch.

Store at controlled room temperature: 59° to 86°F (15° to 30°C).

17 PATIENT COUNSELING INFORMATION

Advise the patient to read the FDA-approved patient labeling (Patient Information).

Before inserting Paragard, counsel patients on the following:

Sexually Transmitted Infections: Advise patients that Paragard does not protect against HIV infection and other sexually transmitted diseases.

Ectopic Pregnancy: Advise patients to report pregnancies and be evaluated immediately, as a pregnancy with Paragard in place is more likely to be an ectopic pregnancy, and the risks of ectopic pregnancy include the loss of fertility [see Warnings and Precautions (5.1)].

Intrauterine Pregnancy: Advise patients to report pregnancies and be evaluated immediately, as an intrauterine pregnancy with Paragard in place, may result in septic abortion, with septicemia, septic shock, and possible death. Septic abortion typically requires hospitalization and treatment with intravenous antibiotics. Septic abortion may result in spontaneous abortion or a medical indication for pregnancy termination. A hysterectomy may be required if severe infection of the uterus occurs, which will result in permanent infertility. If Paragard remains in the uterus during a pregnancy, there is an increased risk of miscarriage, sepsis, premature labor and premature delivery. Advise patients that a pregnancy must be followed closely and advise patients to report immediately any symptom, such as flu- like symptoms, fever, chills, cramping, pain, bleeding, vaginal discharge or leaking of fluid, or any other symptom that suggests complications of the pregnancy [see Warnings and Precautions (5.2)].

Sepsis: Advise patients that sepsis may occur after insertion of Paragard and to seek immediate treatment for fever and pelvic pain that occurs soon after insertion, as untreated sepsis can result in death [see Warnings and Precautions (5.3)].

Pelvic Inflammatory Disease: Advise patients that pelvic inflammatory disease (PID) may occur after insertion of Paragard and that PID can cause tubal damage leading to ectopic pregnancy or infertility, or can necessitate hysterectomy, or cause death. Advise patients to recognize and report promptly any symptoms of PID including development of menstrual disorders (prolonged or heavy bleeding), unusual vaginal discharge, abdominal or pelvic pain or tenderness, dyspareunia, chills, and fever [see Warnings and Precautions (5.4)].

Embedment, Perforation, and Expulsion: Advise patients regarding the risks of embedment, perforation, and expulsion and inform patients that in some cases, removal of Paragard may be difficult and surgical removal may be necessary. Inform patients that perforation can cause infection, scarring, damage to other organs, pain, or infertility. Inform patients that excessive pain or vaginal bleeding during IUS placement, worsening pain or bleeding after placement, or the inability to feel the IUS strings may occur with IUS perforation and expulsion. There is no protection from pregnancy if Paragard is displaced or expelled [see Warnings and Precautions (5.5, 5.6, 5.7).].

Bleeding Pattern Alterations: Advise patients that heavier or longer periods and spotting between periods may occur. Instruct patients to report continued or severe symptoms to their healthcare provider [see Warnings and Precautions (5.9)].

Checking for Paragard: Advise patients to check that Paragard is still in the uterus by reaching up to the top of the vagina with clean fingers to feel the two threads. Inform patients not to pull on the threads, which could displace Paragard. Advise patients to promptly report if there are changes in the length of the two threads, if they cannot locate the threads, or they can feel any other part of Paragard besides the threads.

Magnetic Resonance Imaging (MRI) Safety Information: Inform patients that Paragard can be safely scanned with MRI only under specific conditions. Instruct patients who will have an MRI to tell their healthcare provider that they have Paragard [see Warnings and Precautions (5.10)].

Medical Diathermy: Instruct patients to tell their healthcare provider that they have Paragard prior to undergoing medical diathermy [see Warnings and Precautions (5.11)].

Other Important Information:

1. Advise patients to contact their healthcare provider if any of the following occur:

- Pelvic pain or pain during sex
- Unusual vaginal discharge or genital sores
- Possible exposure to STIs
- HIV positive seroconversion in herself or her partner
- Severe or prolonged vaginal bleeding
- Missed period

2. Advise patients that they may use tampons or pads while wearing Paragard.

Manufactured by:
CooperSurgical, Inc.
Trumbull, CT 06611

PATIENT INFORMATION
PARAGARD® ('par-uh-gahrd)
(intrauterine copper contraceptive)

Paragard does not protect against HIV infection (AIDS) or other sexually transmitted infections (STIs).
Read this Patient Information carefully before you decide if Paragard is right for you. This information does not take the place of talking with your gynecologist or other healthcare provider who specializes in women’s health. If you have any questions about Paragard, ask your healthcare provider. You should also learn about other birth control methods to choose the one that is best for you.

What is Paragard?

- Paragard is a copper-releasing system that is placed in your uterus by your healthcare provider to prevent pregnancy for up to 10 years.
- Paragard can be removed by your healthcare provider at any time.
- Paragard does not contain any hormones.
- Paragard can be used whether or not you have given birth to a child.

Paragard is a small, flexible plastic “T” shaped intrauterine system with copper wrapped around the stem and placed on arms of the “T”. Two thin white threads are attached to the stem (lower end) of Paragard. The threads are the only part of Paragard you can feel when Paragard is in your uterus; however, unlike a tampon string, the threads do not extend outside of your body.

What if I need birth control for more than 10 years?
Paragard must be removed on or before 10 years from the date of insertion. Your healthcare provider can place a new Paragard during the same office visit if you choose to continue using Paragard.

What if I want to stop using Paragard?
Paragard is intended for use up to 10 years, but you can stop using Paragard at any time by asking your healthcare provider to remove it. You could become pregnant as soon as Paragard is removed; however, if you do not want to become pregnant you should use another method of birth control. Talk to your healthcare provider about the best birth control methods for you.

What if I change my mind about birth control and want to become pregnant in less than 10 years?
Your healthcare provider can remove Paragard at any time before the 10 years after placement. You may become pregnant as soon as Paragard is removed.

How does Paragard work?
Paragard works by preventing sperm from reaching the egg, preventing sperm from fertilizing the egg, or possibly preventing attachment (implantation) in the uterus. Paragard does not stop your ovaries from making an egg (ovulating) each month.

How well does Paragard work for contraception?
The following chart shows the chance of getting pregnant for women who use different methods of birth control. Each box on the chart contains a list of birth control methods that are similar in effectiveness. The most effective methods are at the top of the chart. The box on the bottom of the chart shows the chance of getting pregnant for women who do not use birth control and are trying to get pregnant.
Paragard, an intrauterine system (IUS), is in the box at the top of the chart.

Who might use Paragard?
You might choose Paragard if you:

- want long-term birth control that provides a low chance of getting pregnant (less than 1 in 100)
- want birth control that works continuously for up to 10 years
- want birth control that is reversible
- want a birth control method that you do not need to take daily
- are willing to use a birth control method that is inserted in the uterus
- want birth control that does not contain hormones

Do not use Paragard if you:

- are or might be pregnant
- have a condition of the uterus that changes the shape of the uterine cavity, such as large fibroid tumors
- have an untreated pelvic infection called pelvic inflammatory disease (PID) now
- have had an infection in your uterus after a pregnancy or abortion in the past 3 months
- can get infections easily. For example, if you:
  - have problems with your immune system
  - have multiple sexual partners or your partner has multiple sexual partners
  - use or abuse intravenous drugs
- have or suspect you might have cancer of the uterus or cervix
- have unexplained bleeding from your vagina
- have an untreated lower genital infection now in your cervix
- have Wilson’s disease (a disorder in how the body handles copper)
- are allergic to copper, polyethylene, or barium sulfate
- have an intrauterine system in your uterus already

Before having Paragard placed, tell your healthcare provider if you have:

- any of the conditions listed above
- slow heart beat (bradycardia)
- dizziness (syncope)
- seizures
- recently had a baby or if you are breastfeeding
- AIDS, HIV, or any other sexually transmitted infection

How is Paragard placed?
Paragard is placed in your uterus during an in-office visit.
First, your healthcare provider will examine your pelvis to find the exact position of your uterus. Your healthcare provider will then cleanse your vagina and cervix with an antiseptic solution and then, measure your uterus. Your healthcare provider will then slide a plastic tube containing Paragard into your uterus. The tube is removed, leaving Paragard inside your uterus. Two white threads will extend into your vagina. The threads are trimmed so they are just long enough for you to feel with your fingers when doing a self-check. As Paragard goes in, you may feel cramping or pinching. You may have some bleeding. Some women feel faint, nauseated, or dizzy for a few minutes afterwards. Your healthcare provider may ask you to lie down until you are feeling better, and to get up slowly.

Should I check that Paragard is in place?
Yes, you should check that Paragard is in proper position by feeling the threads. It is a good habit to do this 1 time a month. Your healthcare provider should teach you how to check that Paragard is in place. First, wash your hands with soap and water. You can check by reaching up to the top of your vagina with clean fingers to feel the 2 threads. Do not pull on the threads.
If you feel changes in the length of the 2 threads, you cannot feel the threads, or you can feel any other part of Paragard other than the threads, Paragard may not be in the right position and may not prevent pregnancy. Use back-up birth control (such as condoms or spermicide) and ask your healthcare provider to check that Paragard is still in the right place.
If Paragard is accidentally removed, you may be at risk of pregnancy, and should talk to a healthcare provider.

How soon after placement of Paragard should I return to my healthcare provider?
Call your healthcare provider if you have any questions or concerns (see “When should I call my healthcare provider?”). Otherwise you should return to your healthcare provider for a follow-up visit after your first menses after Paragard is placed to make sure that Paragard is in the right position.

What if I become pregnant while using Paragard?
Call your healthcare provider right away if you think you may be pregnant. If you get pregnant while using Paragard, you may have an ectopic pregnancy. This means the pregnancy is not in your uterus. Unusual vaginal bleeding or abdominal pain especially with missed periods may be a sign of ectopic pregnancy.
Ectopic pregnancy is a medical emergency that often requires surgery. Ectopic pregnancy can cause internal bleeding, infertility and even death.
There are also risks if you get pregnant while using Paragard and the pregnancy is in the uterus. Severe infection, miscarriage, premature delivery, and even death can occur with pregnancies that continue with an intrauterine device (IUD). Because of this, your healthcare provider may try to remove Paragard, even though removing it may cause a miscarriage. If Paragard cannot be removed, talk with your healthcare provider about the benefits and risks of continuing the pregnancy.
If you continue your pregnancy see your healthcare provider regularly. Call your healthcare provider right away if you get flu-like symptoms, fever, chills, cramping, pain, bleeding, vaginal discharge, or fluid leaking from your vagina. These may be signs of infection.
It is not known if Paragard can cause long-term effects on the fetus if it stays in place during a pregnancy.

How will Paragard change my periods?
Your period may become heavier and longer. You may also have frequent spotting between periods.

Is it safe to breastfeed while using Paragard?
You may use Paragard when you are breastfeeding. The risk of Paragard becoming attached to (embedded) or going through the wall of the uterus is increased if Paragard is placed while you are breastfeeding.

Will Paragard interfere with sexual intercourse?
You and your partner should not feel Paragard during intercourse. Paragard is placed in the uterus, not in the vagina. Sometimes your partner may feel the threads. If this occurs, or if you or your partner experience pain during sex, talk with your healthcare provider.

Can I have an MRI with Paragard in place?
Paragard can be safely scanned with MRI only under specific conditions. Before you have an MRI, tell your healthcare provider that you have Paragard, an intrauterine device (IUD), in place.

Before you have a medical procedure using heat therapy tell your healthcare provider that you have Paragard in place.

What are the possible side effects of Paragard? Paragard can cause serious side effects, including:

- ectopic pregnancy and intrauterine pregnancy risks: There are risks if you become pregnant while using Paragard (see “What if I become pregnant while using Paragard?”).
- life-threatening infection: Life-threatening infection can occur within the first few days after Paragard is placed. Call your healthcare provider immediately if you develop severe pain or fever shortly after Paragard is placed.
- pelvic inflammatory disease (PID) or endometritis: Some IUS users get a serious pelvic infection called pelvic inflammatory disease (PID) or endometritis. PID and endometritis are usually sexually transmitted. You have a higher chance of getting PID and endometritis if you or your partner has sex with other partners. PID and endometritis can cause serious problems such as infertility, ectopic pregnancy, and pelvic pain that does not go away. PID and endometritis are usually treated with antibiotics. More serious cases of PID or endometritis may require surgery. A hysterectomy (removal of the uterus) is sometimes needed. In rare cases, infections that start as PID can even cause death.
  Tell your healthcare provider right away if you have any of these signs of PID or endometritis: low abdominal (stomach area) or pelvic pain, pelvic tenderness, painful sex, unusual or bad smelling vaginal discharge, chills, long-lasting or heavy bleeding, fever, genital lesions or sores.
- embedment: Paragard may become attached to (embedded) the wall of the uterus. This may make it hard to remove Paragard. Surgery may sometimes be needed to remove Paragard.
- perforation: Paragard may go through the wall of the uterus. This is called perforation. If this occurs, Paragard may no longer prevent pregnancy. If perforation occurs, Paragard may move outside the uterus and cause internal scarring, infection, damage to other organs, pain, or infertility and you may need surgery to have Paragard removed. Excessive pain or vaginal bleeding during placement of Paragard, pain or bleeding that gets worse after placement, or not being able to feel the threads may happen with perforation. You are not protected from pregnancy if Paragard moves outside the wall of the uterus. The risk of perforation is increased in breastfeeding women.
- expulsion: Paragard may partially or completely fall out of the uterus by itself. This is called expulsion. Expulsion occurs in about 2 out of 100 women. Excessive pain, vaginal bleeding during placement of Paragard, pain that gets worse, bleeding after placement, or not being able to feel the threads may happen with expulsion. You are not protected from pregnancy if Paragard is expelled.
- changes in bleeding: You may have heavier and longer periods with spotting in between. Sometimes the bleeding is heavier than usual at first. Call your healthcare provider if the bleeding remains heavier or longer and spotting continues.

- reactions after placement or removal: Some women have had reactions such as dizziness (syncope), slowed heart rate (bradycardia), or seizures, immediately after Paragard was placed or removed. This happened especially in women who have had these conditions before.

Common side effects of Paragard include:

- anemia (low red blood cell count)

- backache

- painful periods

- pain during sex

- expulsion (complete or partial)

- vaginal discharge

- prolonged periods

- spotting

- pain and cramping

- vaginal irritation

This is not a complete list of possible side effects with Paragard. For more information, ask your healthcare provider. Tell your healthcare provider about any side effect that bothers you or does not go away.
Call your doctor for medical advice about side effects. You may report side effects to FDA at 1-800- FDA-1088.

After Paragard has been placed, when should I call my healthcare provider?
Call your healthcare provider if you have any concerns about Paragard. Be sure to call if you:

- think you are pregnant
- have pelvic pain or pain during sex
- have unusual vaginal discharge or genital sores
- have unexplained fever, flu-like symptoms or chills
- might be exposed to sexually transmitted infections (STIs)
- are concerned that Paragard may have been expelled (came out)
- cannot feel Paragard’s threads or can feel the threads are much longer
- can feel any other part of the Paragard besides the threads
- become HIV positive or your partner becomes HIV positive
- have severe, bleeding that lasts a long time, or bleeding that concerns you
- miss a menstrual period

General information about the safe and effective use of Paragard.
Medicines are sometimes prescribed for purposes other than those listed in a Patient Information leaflet. You can ask your healthcare provider for information about Paragard that is written for health professionals.

Paragard and its components are not made with natural rubber latex.

Paragard® is a registered trademark of CooperSurgical, Inc. The other brands listed are trademarks of their respective owners. Manufactured by:
CooperSurgical, Inc. Trumbull, CT 06611
For more information, call CooperSurgical, Inc. at 1-877-727-2427.

This Patient Information has been approved by the U.S. Food and Drug Administration

Principal Display Panel

Cooper Surgical®

Paragard® T380A

intrauterine copper contraceptive

1 UNIT

Each unit wound with approximately 176 mg of copper wire. In addition, a single copper sleeve is swaged on each of the two transverse arms. Each sleeve contains approximately 68.7 mg of copper. The total surface area of copper on the device is 380 ± 23mm^2.

IMPORTANT: Read the Preparation Instructions and Insertion Procedure before initiating Paragard insertion. To be inserted in the uterus only by a licensed clinician or under the supervision of a physician. See detailed instructions in the Prescribing Information.

NOTE: Patient Information is provided with each unit. Please ensure the Patient Information is provided to and reviewed with each patient before insertion. Store at controlled room temperature: 59º to 86ºF (15° to 30°C).

CooperSurgical, Inc. | 95 Corporate Drive | Trumbull, CT 06611 USA

RX ONLY

NDC 59365-5129-1